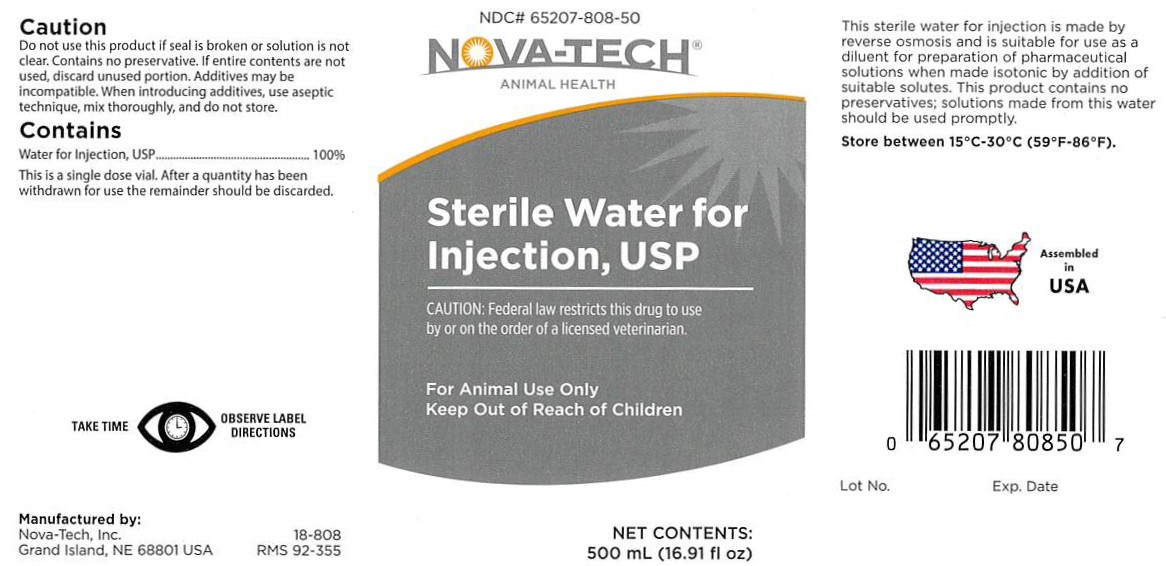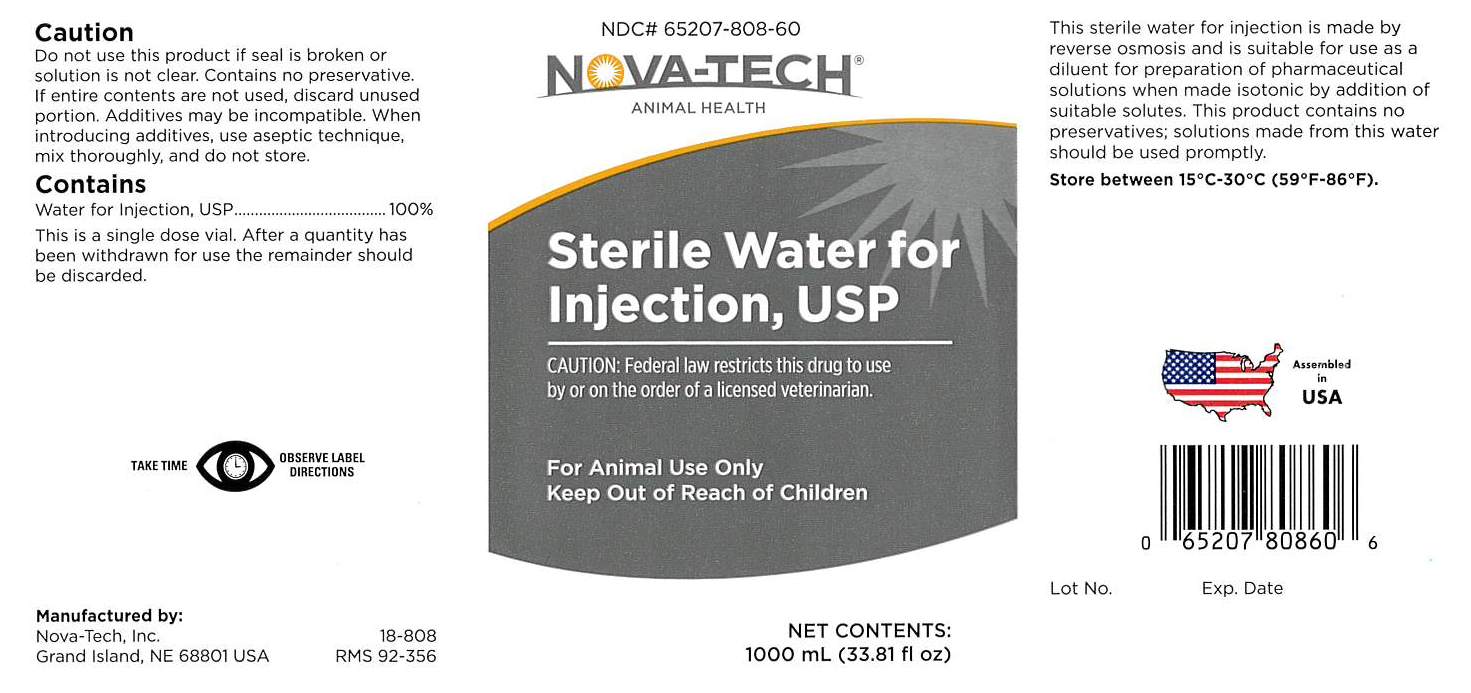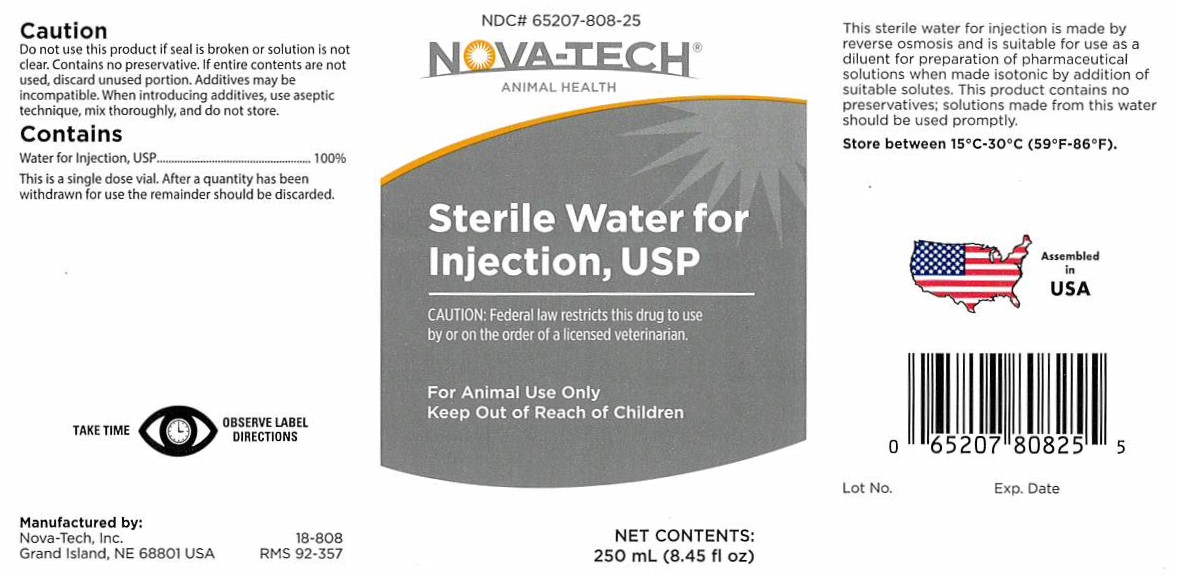 DRUG LABEL: Sterile Water
NDC: 65207-808 | Form: INJECTION
Manufacturer: Nova-Tech, Inc.
Category: animal | Type: PRESCRIPTION ANIMAL DRUG LABEL
Date: 20200312

ACTIVE INGREDIENTS: WATER 1000 mL/1000 mL

Sterile Water For Injection, USP

CAUTION:

Do not use this product if seal is broken or solution is not clear. Contains no preservative. If entire contents are not used, discard unused portion. Additives may be incompatible. When introducing additives, use aseptic technique, mix thoroughly, and do not store.

CONTAINS:

Water For Injection, USP.................100%

This is a single dose vial. After a quantity has been withdrawn for use the remainder should be discarded.

GENERAL PRECAUTIONS

TAKE TIME OBSERVE LABEL DIRECTIONS

INFORMATION FOR OWNERS/CAREGIVERS

Manufactured by:

Nova-Tech, Inc.

Grand Island, NE 68801 USA

18-808

RMS 92-356

Assembled in USA

Lot No.

Exp. Date

GENERAL PRECAUTIONS

FOR ANIMAL USE ONLY

KEEP OUT OF REACH OF CHILDREN

CAUTION:

Federal law restricts this drug to use by or on the order of a licensed veterinarian.

INDICATIONS AND USAGE

This sterile water for injection is made by reverse osmosis and is suitable for use as a diluent for preparation of pharmaceutical solutions when made isotonic by addition of suitable solutes. This product contains no preservatives; solutions made from this water should be used promptly.

STORAGE AND HANDLING

Store between 15°C - 30°C (59°F - 86°F)